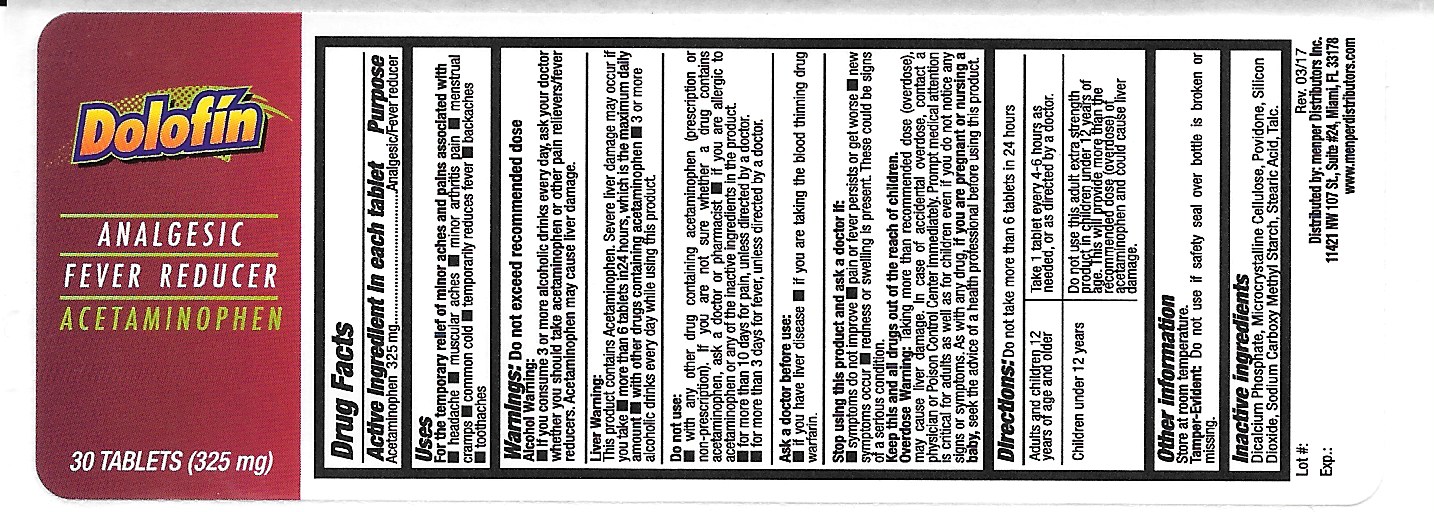 DRUG LABEL: Dolofin
NDC: 53145-420 | Form: TABLET
Manufacturer: Menper Distributors Inc.
Category: otc | Type: HUMAN OTC DRUG LABEL
Date: 20171024

ACTIVE INGREDIENTS: ACETAMINOPHEN 325 mg/1 1
INACTIVE INGREDIENTS: ANHYDROUS DIBASIC CALCIUM PHOSPHATE; MICROCRYSTALLINE CELLULOSE; POVIDONE; SILICON DIOXIDE; CARBOXYMETHYLCELLULOSE SODIUM; STARCH, CORN; STEARIC ACID; TALC

Active Ingredient (in each tablet)

Acetaminophen 325 mg

Purpose

Pain reliever/Fever reducer

Uses

For the temporary relief of minor aches and pains associated with

- headache
- muscular aches
- minor arthritis pain
- menstrual cramps
- common cold
- temporarily reduces fever
- backaches
- toothaches

Warnings:

Alcohol warning:

- if you consume 3 or more alcoholic drinks every day, ask your doctor whether you should take acetaminophen or other pain relievers/fever reducers. Acetaminophen may cause liver damage.

Liver warning:

This product contains acetaminophen. Sever liver damage may occur if you take

- more than 6 tablets in 24 hours, which is the maximum daily amount
- with other drugs containing acetaminophen
- 3 or more alcoholic drinks every day.

Do not use:

- with any other drug conatining acetaminophen (prescription or non-prescription). If you are not sure whether a drug contains acetaminophen, ask a doctor or pharmacist.
- If you are allergic to acetaminophen or any of the inactive ingredients in the product.
- for more than 10 days for pain, unless directed by a doctor.
- for more than 3 days for fever, unless directed by a doctor.

Ask a doctor before use

- if you have liver disease
- if you are taking the blood thinning drug warfarin.

Stop using this product and ask a doctor if:

- symptoms do not improve
- pain or fever persists or get worse
- New symptoms occur
- Redness or swelling is present
- These could be signs of a serious condition

PREGNANCY OR BREAST FEEDING

As with any drug, if you are pregnant or nursing a baby, seek the advice of a health professional before using this product.

KEEP OUT OF REACH OF CHILDREN

Keep this and all drugs out of the reach of children

Overdose warning: In case of overdose, get medical help or contact a Poison Control Center right away. (1-800-222-1222) Quick medical attention is critical for adults as well as for children even if you do not notice any signs or symptoms.

Directions:

- Do not take more than 6 tablets in 24 hours

Adults and children12 years and over | Take 1 tablet every 4-6 hours as needed, or as directed by a doctor.
Children under 12 years | Do not use this adult extra strength product in children under 12 years of age. This will provide more than the recommended dose (overdose) of acetaminophen and could cause liver damage.

INACTIVE INGREDIENT

Inactive ingredients Dicalcium phosphate, microcrystalline cellulose, povidone, silicon dioxide, sodium carboxy methyl starch, stearic acid, talc

QUESTIONS

Questions: Call 1-800-560-5223 M-F 9AM - 4PM Eastern